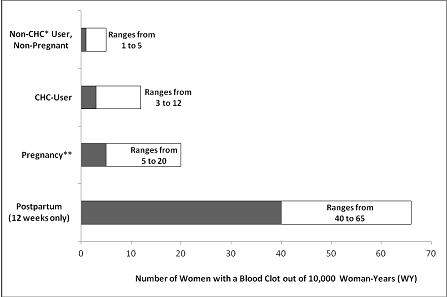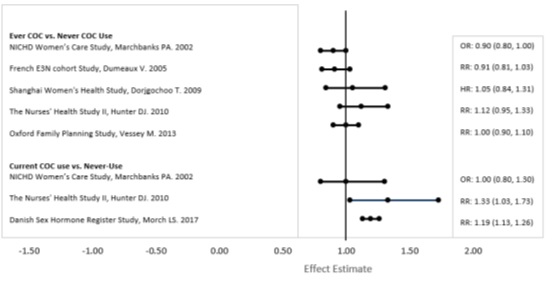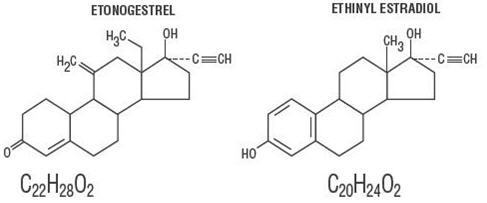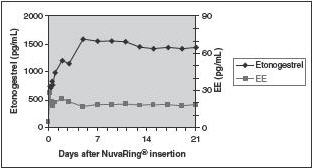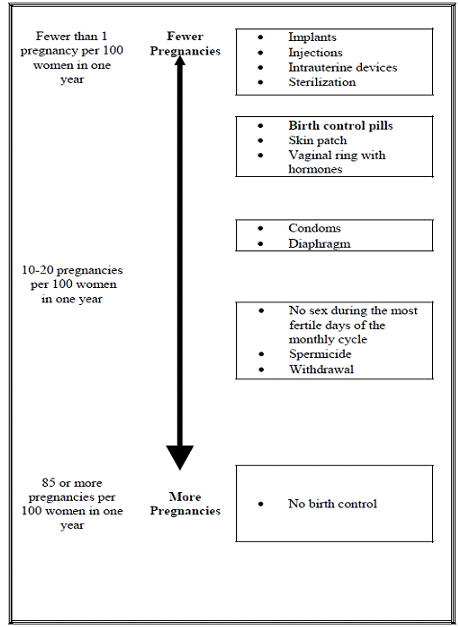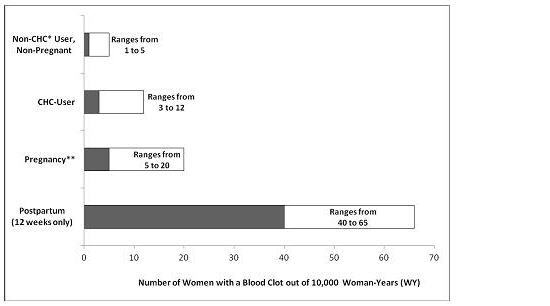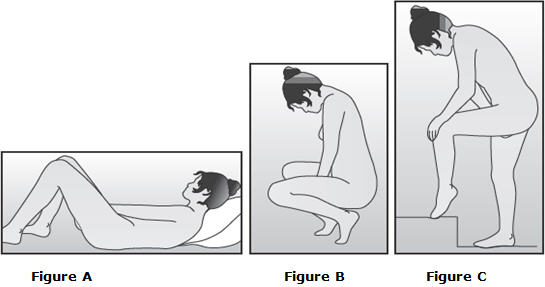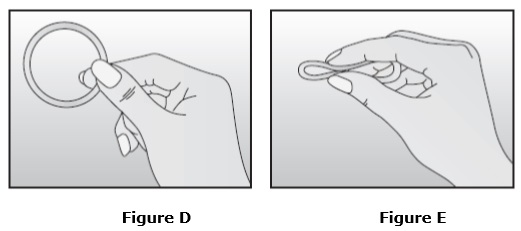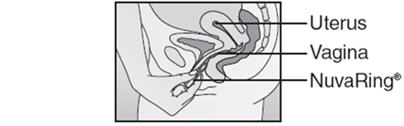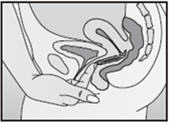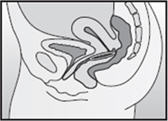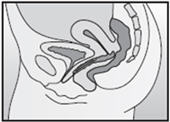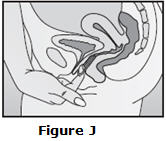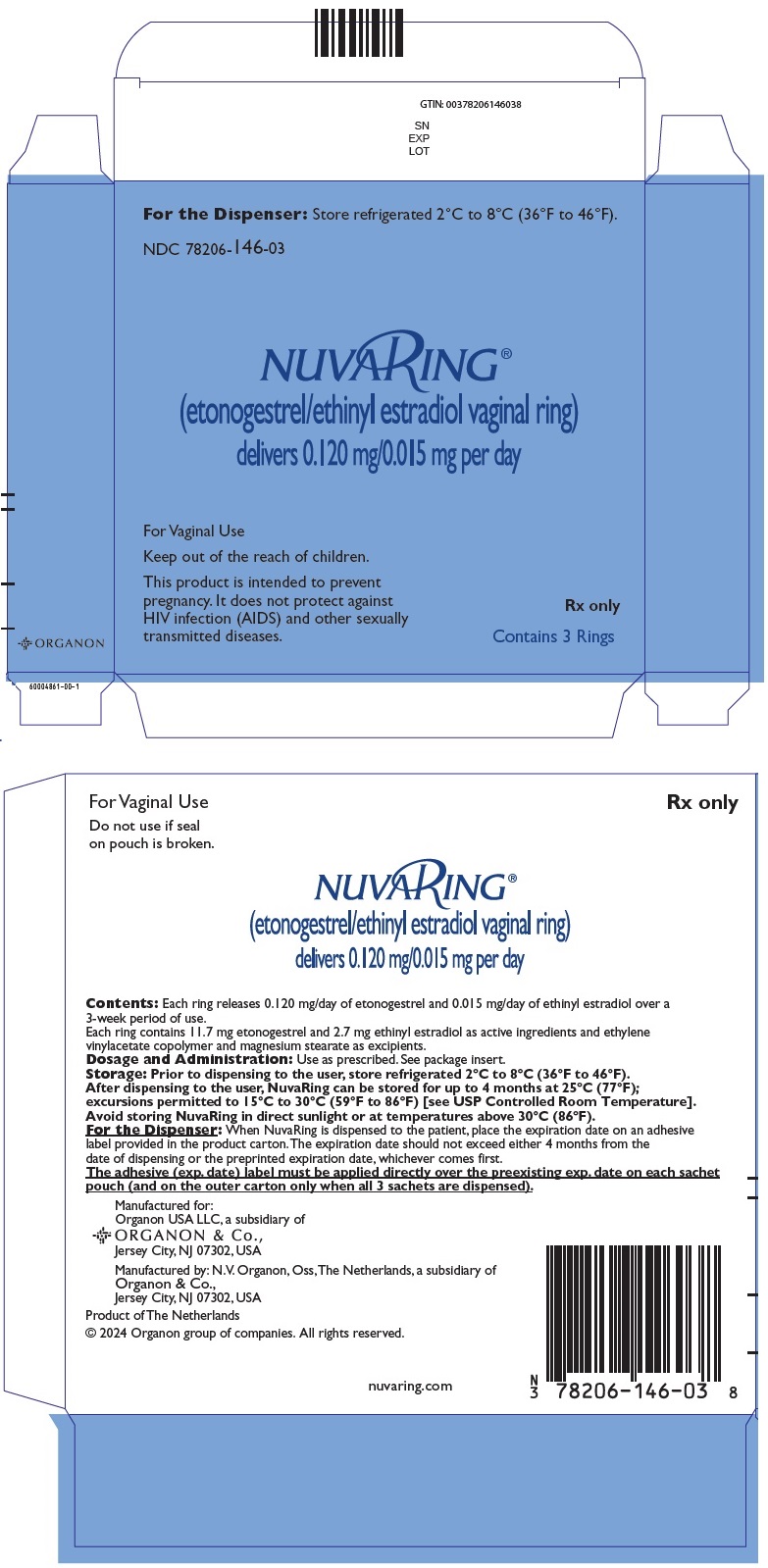 DRUG LABEL: NuvaRing
NDC: 78206-146 | Form: INSERT, EXTENDED RELEASE
Manufacturer: Organon LLC
Category: prescription | Type: HUMAN PRESCRIPTION DRUG LABEL
Date: 20251114

ACTIVE INGREDIENTS: ETONOGESTREL 0.12 mg/1 d; ETHINYL ESTRADIOL 0.015 mg/1 d
INACTIVE INGREDIENTS: ETHYLENE-VINYL ACETATE COPOLYMER (28% VINYL ACETATE); ETHYLENE-VINYL ACETATE COPOLYMER (9% VINYLACETATE); MAGNESIUM STEARATE

HIGHLIGHTS OF PRESCRIBING INFORMATION

These highlights do not include all the information needed to use NuvaRing safely and effectively. See full prescribing information for NuvaRing.
NuvaRing® (etonogestrel/ethinyl estradiol vaginal ring)
Initial U.S. Approval: 2001

RECENT MAJOR CHANGES

Warnings and Precautions (5.4) | 6/2024

WARNING: CIGARETTE SMOKING AND SERIOUS CARDIOVASCULAR EVENTS

See full prescribing information for complete boxed warning.

- Women over 35 years old who smoke should not use NuvaRing. (4)
- Cigarette smoking increases the risk of serious cardiovascular events from combination hormonal contraceptive (CHC) use. (4)

1 INDICATIONS AND USAGE

NuvaRing is an estrogen/progestin combination hormonal contraceptive (CHC) indicated for use by women to prevent pregnancy. (1)

2 DOSAGE AND ADMINISTRATION

One NuvaRing is inserted in the vagina. The ring must remain in place continuously for three weeks, followed by a one-week ring-free interval. (2)

3 DOSAGE FORMS AND STRENGTHS

NuvaRing is a polymeric vaginal ring containing 11.7 mg etonogestrel and 2.7 mg ethinyl estradiol, which releases on average 0.12 mg/day of etonogestrel and 0.015 mg/day of ethinyl estradiol. (3)

4 CONTRAINDICATIONS

- A high risk of arterial or venous thrombotic diseases (4)
- Breast cancer (4)
- Liver tumors or liver disease (4)
- Undiagnosed abnormal uterine bleeding (4)
- Pregnancy (4)
- Hypersensitivity, including anaphylaxis and angioedema, to any of the components of NuvaRing (4)
- Co-administration with Hepatitis C drug combinations containing ombitasvir/paritaprevir/ritonavir, with or without dasabuvir (4)

5 WARNINGS AND PRECAUTIONS

- Vascular risks: Stop NuvaRing use if a thrombotic event occurs. Stop NuvaRing use at least 4 weeks before and through 2 weeks after major surgery. Start no earlier than 4 weeks after delivery, in women who are not breastfeeding. (5.1)
- Toxic Shock Syndrome (TSS): If patient exhibits signs or symptoms of TSS, consider the possibility of this diagnosis and initiate appropriate medical evaluation and treatment. (5.2)
- Liver disease: Discontinue NuvaRing use if jaundice develops. (5.3)
- High blood pressure: If used in women with well-controlled hypertension, monitor blood pressure and stop NuvaRing use if blood pressure rises significantly. (5.5)
- Carbohydrate and lipid metabolic effects: Monitor prediabetic and diabetic women. Consider an alternate contraceptive method for women with uncontrolled dyslipidemia. (5.9)
- Headache: Evaluate significant change in headaches and discontinue NuvaRing use if indicated. (5.10)
- Uterine bleeding: Evaluate irregular bleeding or amenorrhea. (5.11)

6 ADVERSE REACTIONS

The most common adverse reactions (≥2%) in clinical trials were: vaginitis, headache (including migraine), mood changes (e.g., depression, mood swings, mood altered, depressed mood, affect lability), device-related events (e.g., expulsion/discomfort/foreign body sensation), nausea/vomiting, vaginal discharge, increased weight, vaginal discomfort, breast pain/discomfort/tenderness, dysmenorrhea, abdominal pain, acne, and decreased libido. (6)

To report SUSPECTED ADVERSE REACTIONS, contact Organon USA LLC, a subsidiary of Organon & Co., at 1-844-674-3200 or FDA at 1-800-FDA-1088 or www.fda.gov/medwatch.

7 DRUG INTERACTIONS

Drugs or herbal products that induce certain enzymes, such as CYP3A4, may decrease the effectiveness of CHCs or increase breakthrough bleeding. Counsel patients to use a back-up or alternative method of contraception when enzyme inducers are used with CHCs. (7)

8 USE IN SPECIFIC POPULATIONS

- Nursing mothers: Not recommended; can decrease milk production. (8.2)

FULL PRESCRIBING INFORMATION

WARNING: CIGARETTE SMOKING AND SERIOUS CARDIOVASCULAR EVENTS

Cigarette smoking increases the risk of serious cardiovascular events from combination hormonal contraceptive (CHC) use. This risk increases with age, particularly in women over 35 years of age, and with the number of cigarettes smoked. For this reason, CHCs, including NuvaRing, should not be used by women who are over 35 years of age and smoke. [See Contraindications (4).]

1 INDICATIONS AND USAGE

FOR VAGINAL USE ONLY

NuvaRing® is indicated for use by females of reproductive age to prevent pregnancy.

2 DOSAGE AND ADMINISTRATION

2.1 How to Use NuvaRing

To achieve maximum contraceptive effectiveness, NuvaRing must be used as directed [see Dosage and Administration (2.2)]. One NuvaRing is inserted in the vagina. The ring is to remain in place continuously for three weeks. It is removed for a one-week break, during which a withdrawal bleed usually occurs. A new ring is inserted one week after the last ring was removed.

The user can choose the insertion position that is most comfortable to her, for example, standing with one leg up, squatting, or lying down. The ring is to be compressed and inserted into the vagina. The exact position of NuvaRing inside the vagina is not critical for its function. The vaginal ring must be inserted on the appropriate day and left in place for three consecutive weeks. This means that the ring should be removed three weeks later on the same day of the week as it was inserted and at about the same time.

NuvaRing can be removed by hooking the index finger under the forward rim or by grasping the rim between the index and middle finger and pulling it out. The used ring should be placed in the sachet (foil pouch) and discarded in a waste receptacle out of the reach of children and pets (do not flush in toilet).

After a one-week break, during which a withdrawal bleed usually occurs, a new ring is inserted on the same day of the week as it was inserted in the previous cycle. The withdrawal bleed usually starts on Day 2-3 after removal of the ring and may not have finished before the next ring is inserted. In order to maintain contraceptive effectiveness, the new ring must be inserted exactly one week after the previous one was removed even if menstrual bleeding has not finished.

2.2 How to Start Using NuvaRing

IMPORTANT: Consider the possibility of ovulation and conception prior to the first use of NuvaRing.

No Hormonal Contraceptive Use in the Preceding Cycle:

The woman should insert NuvaRing on the first day of her menstrual bleeding. NuvaRing may also be started on Days 2-5 of the woman's cycle, but in this case a barrier method, such as male condoms with spermicide, should be used for the first seven days of NuvaRing use in the first cycle.

Changing From a CHC:

The woman may switch from her previous CHC on any day, but at the latest on the day following the usual hormone-free interval, if she has been using her hormonal method consistently and correctly, or if it is reasonably certain that she is not pregnant.

Changing From a Progestin-Only Method (progestin-only pill [POP], Implant, or Injection or a Progestin-Releasing Intrauterine System [IUS]):

The woman may switch from the POP on any day; instruct her to start using NuvaRing on the day after she took her last POP. She should switch from an implant or the IUS on the day of its removal, and from an injectable on the day when the next injection would be due. In all of these cases, the woman should use an additional barrier method such as a male condom with spermicide, for the first seven days.

Use After Abortion or Miscarriage:

The woman may start using NuvaRing within the first five days following a complete first trimester abortion or miscarriage, and she does not need to use an additional method of contraception. If use of NuvaRing is not started within five days following a first trimester abortion or miscarriage, the woman should follow the instructions for "No Hormonal Contraceptive Use in the Preceding Cycle." In the meantime, she should be advised to use a non-hormonal contraceptive method.

Start NuvaRing no earlier than four weeks after a second trimester abortion or miscarriage, due to the increased risk of thromboembolism. [See Contraindications (4) and Warnings and Precautions (5.1).]

Following Childbirth:

The use of NuvaRing may be initiated no sooner than four weeks postpartum in women who elect not to breastfeed, due to the increased risk of thromboembolism in the postpartum period. [See Contraindications (4) and Warnings and Precautions (5.1).]

Advise women who are breastfeeding not to use NuvaRing but to use other forms of contraception until the child is weaned.

If a woman begins using NuvaRing postpartum, instruct her to use an additional method of contraception, such as male condoms with spermicide, for the first seven days. If she has not yet had a period, consider the possibility of ovulation and conception occurring prior to initiation of NuvaRing.

2.3 Deviations from the Recommended Regimen

To prevent loss of contraceptive efficacy, advise women not to deviate from the recommended regimen. NuvaRing should be left in the vagina for a continuous period of three weeks. Advise women to regularly check for the presence of NuvaRing in the vagina (for example, before and after intercourse).

Inadvertent Removal or Expulsion:

NuvaRing can be accidentally expelled, for example, while removing a tampon, during intercourse, or with straining during a bowel movement. NuvaRing should be left in the vagina for a continuous period of three weeks. If the ring is accidentally expelled and is left outside of the vagina for less than three hours, contraceptive efficacy is not reduced. NuvaRing can be rinsed with cool to lukewarm (not hot) water and reinserted as soon as possible, but at the latest within three hours. If NuvaRing is lost, a new vaginal ring should be inserted and the regimen should be continued without alteration.

If NuvaRing is out of the vagina for more than three continuous hours:

During Weeks 1 and 2: Contraceptive efficacy may be reduced. The woman should reinsert the ring as soon as she remembers. A barrier method such as male condoms with spermicides must be used until the ring has been used continuously for seven days.

During Week 3: The woman should discard that ring. One of the following two options should be chosen:

1. Insert a new ring immediately. Inserting a new ring will start the next three-week use period. The woman may not experience a withdrawal bleed from her previous cycle. However, breakthrough spotting or bleeding may occur.
2. Insert a new ring no later than seven days from the time the previous ring was removed or expelled, during which time she may have a withdrawal bleed. This option should only be chosen if the ring was used continuously for at least seven days prior to inadvertent removal/expulsion.

In either case, a barrier method such as male condoms with spermicides must be used until the new ring has been used continuously for seven days.

If NuvaRing was out of the vagina for an unknown amount of time, the possibility of pregnancy should be considered. A pregnancy test should be performed prior to inserting a new ring.

Prolonged Ring-Free Interval:

If the ring-free interval has been extended beyond one week, consider the possibility of pregnancy, and an additional method of contraception, such as male condoms with spermicide, MUST be used until NuvaRing has been used continuously for seven days.

Prolonged Use of NuvaRing:

If NuvaRing has been left in place for up to one extra week (i.e., up to four weeks total), the woman will remain protected. NuvaRing should be removed and the woman should insert a new ring after a one-week ring-free interval.

If NuvaRing has been left in place for longer than four weeks, instruct the woman to remove the ring, and rule out pregnancy. If pregnancy is ruled out, NuvaRing may be restarted, and an additional method of contraception, such as male condoms with spermicide, MUST be used until a new NuvaRing has been used continuously for seven days.

Ring Breakage:

There have been reported cases of NuvaRing disconnecting at the weld joint. This is not expected to affect the contraceptive effectiveness of NuvaRing. In the event of a disconnected ring, vaginal discomfort or expulsion (slipping out) is more likely to occur. Vaginal injury associated with ring breakage has been reported [see Adverse Reactions (6.2)].

If a woman discovers that her NuvaRing has disconnected, she should discard the ring and replace it with a new ring.

2.4 In the Event of a Missed Menstrual Period

1. If the woman has not adhered to the prescribed regimen (NuvaRing has been out of the vagina for more than three hours or the preceding ring-free interval was extended beyond one week), consider the possibility of pregnancy at the time of the first missed period and discontinue NuvaRing use if pregnancy is confirmed.
2. If the woman has adhered to the prescribed regimen and misses two consecutive periods, rule out pregnancy.
3. If the woman has retained one NuvaRing for longer than four weeks, rule out pregnancy.

2.5 Use with Other Vaginal Products

NuvaRing may interfere with the correct placement and position of certain female barrier methods such as a diaphragm, cervical cap or female condom. These methods are not recommended as back-up methods with NuvaRing use.

Pharmacokinetic data show that the use of tampons has no effect on the systemic absorption of the hormones released by NuvaRing.

3 DOSAGE FORMS AND STRENGTHS

NuvaRing (etonogestrel/ethinyl estradiol vaginal ring) is a non-biodegradable, flexible, transparent, colorless to almost colorless, combination contraceptive vaginal ring, with an outer diameter of 54 mm and a cross-sectional diameter of 4 mm. It is made of ethylene vinylacetate copolymers and magnesium stearate, and contains 11.7 mg etonogestrel and 2.7 mg ethinyl estradiol. When placed in the vagina, each ring releases on average 0.120 mg/day of etonogestrel and 0.015 mg/day of ethinyl estradiol over a three-week period of use. NuvaRing is not made with natural rubber latex.

4 CONTRAINDICATIONS

NuvaRing is contraindicated in females who are known to have or develop the following conditions:

- A high risk of arterial or venous thrombotic diseases. Examples include women who are known to:
  - Smoke, if over age 35 [see Boxed Warning and Warnings and Precautions (5.1)]
  - Have deep vein thrombosis or pulmonary embolism, now or in the past [see Warnings and Precautions (5.1)]
  - Have cerebrovascular disease [see Warnings and Precautions (5.1)]
  - Have coronary artery disease [see Warnings and Precautions (5.1)]
  - Have thrombogenic valvular or thrombogenic rhythm diseases of the heart (for example, subacute bacterial endocarditis with valvular disease, or atrial fibrillation) [see Warnings and Precautions (5.1)]
  - Have inherited or acquired hypercoagulopathies [see Warnings and Precautions (5.1)]
  - Have uncontrolled hypertension [see Warnings and Precautions (5.5)]
  - Have diabetes mellitus with vascular disease [see Warnings and Precautions (5.9)]
  - Have headaches with focal neurological symptoms or migraine headaches with aura [see Warnings and Precautions (5.10)]
    - Women over age 35 with any migraine headaches [see Warnings and Precautions (5.10)]
- Liver tumors, benign or malignant or liver disease [see Warnings and Precautions (5.3) and Use in Specific Populations (8.6)]
- Undiagnosed abnormal uterine bleeding [see Warnings and Precautions (5.11)]
- Pregnancy, because there is no reason to use CHCs during pregnancy [see Use in Specific Populations (8.1)]
- Current diagnosis of, or history of, breast cancer, which may be hormone-sensitive [see Warnings and Precautions (5.14)]
- Hypersensitivity reactions, including anaphylaxis and angioedema, to any of the components of NuvaRing [see Warnings and Precautions (5.6) and Adverse Reactions (6)]
- Use of Hepatitis C drug combinations containing ombitasvir/paritaprevir/ritonavir, with or without dasabuvir, due to potential for ALT elevations [see Warnings and Precautions (5.4) and Drug Interactions (7)]

5 WARNINGS AND PRECAUTIONS

5.1 Thromboembolic Disorders and Other Vascular Problems

Stop NuvaRing use if an arterial thrombotic or venous thromboembolic event (VTE) occurs. Stop NuvaRing use if there is unexplained loss of vision, proptosis, diplopia, papilledema, or retinal vascular lesions. Evaluate for retinal vein thrombosis immediately. [See Adverse Reactions (6).]

If feasible, stop NuvaRing at least four weeks before and through two weeks after major surgery or other surgeries known to have an elevated risk of thromboembolism, and during and following prolonged immobilization.

Start NuvaRing no earlier than 4 weeks after delivery, in women who are not breastfeeding. The risk of postpartum thromboembolism decreases after the third postpartum week, whereas the risk of ovulation increases after the third postpartum week.

The use of CHCs increases the risk of VTE. Known risk factors for VTE include smoking, obesity, and family history of VTE, in addition to other factors that contraindicate use of CHCs [see Contraindications (4)].

Two epidemiologic studies^(1, 2, 3) that assessed the risk of VTE associated with the use of NuvaRing are described below.

In these studies, which were required or sponsored by regulatory agencies, NuvaRing users had a risk of VTE similar to Combined Oral Contraceptives (COCs) users (see Table 1 for adjusted hazard ratios). A large prospective, observational study, the Transatlantic Active Surveillance on Cardiovascular Safety of NuvaRing (TASC), investigated the risk of VTE for new users, and women who were switching to or restarting NuvaRing or COCs in a population that is representative of routine clinical users. The women were followed for 24 to 48 months. The results showed a similar risk of VTE among NuvaRing users (VTE incidence 8.3 per 10,000 WY) and women using COCs (VTE incidence 9.2 per 10,000 WY). For women using COCs that did not contain the progestins desogestrel (DSG) or gestodene (GSD), VTE incidence was 8.9 per 10,000 WY.

A retrospective cohort study using data from 4 health plans in the US (FDA-funded Study in Kaiser Permanente and Medicaid databases) showed the VTE incidence for new users of NuvaRing to be 11.4 events per 10,000 WY, for new users of a levonorgestrel (LNG)-containing COC 9.2 events per 10,000 WY, and for users of other COCs available during the course of the study [Includes low-dose COCs containing the following progestins: norgestimate, norethindrone, or levonorgestrel.] 8.2 events per 10,000 WY.

Table 1: Estimates (Hazard Ratios) of Venous Thromboembolism Risk in Users of NuvaRing Compared to Users of Combined Oral Contraceptives (COCs)
Epidemiologic Study (Author, Year of Publication) Population Studied | Comparator Product(s) | Hazard Ratios (HR) (95% CI)
TASC (Dinger, 2012) Initiators, including new users, switchers and restarters | All COCs available during the course of the study [Includes low-dose COCs containing the following progestins: chlormadinone acetate, cyproterone acetate, desogestrel, dienogest, drospirenone, ethynodiol diacetate, gestodene, levonorgestrel, norethindrone, norgestimate, or norgestrel] COCs available excluding DSG- or GSD -containing OCs | HR [Adjusted for age, BMI, duration of use, VTE history] : 0.8 (0.5-1.5) HR: 0.8 (0.4-1.7)
FDA-funded Study in Kaiser Permanente and Medicaid databases (Sidney, 2011)
First use of a combined hormonal contraceptive (CHC) during the study period | COCs available during the course of the study [Includes low-dose COCs containing the following progestins: norgestimate, norethindrone, or levonorgestrel] | HR [Adjusted for age, site, year of entry into study] : 1.1 (0.6-2.2)
 | LNG/0.03 mg ethinyl estradiol | HR: 1.0 (0.5-2.0)

An increased risk of thromboembolic and thrombotic disease associated with the use of CHCs is well-established. Although the absolute VTE rates are increased for users of CHCs compared to non-users, the rates associated with pregnancy are even greater, especially during the post-partum period (see Figure 1).

The frequency of VTE in women using CHCs has been estimated to be 3 to 12 cases per 10,000 women-years.

The risk of VTE is highest during the first year of CHC use and after restarting a CHC following a break of at least four weeks. The risk of VTE due to CHCs gradually disappears after use is discontinued.

Figure 1 shows the risk of developing a VTE for women who are not pregnant and do not use CHCs, for women who use CHCs, for pregnant women, and for women in the postpartum period. To put the risk of developing a VTE into perspective: If 10,000 women who are not pregnant and do not use CHCs are followed for one year, between 1 and 5 of these women will develop a VTE.

Figure 1: Likelihood of Developing a VTE

*CHC=combination hormonal contraception
**Pregnancy data based on actual duration of pregnancy in the reference studies. Based on a model assumption that pregnancy duration is nine months, the rate is 7 to 27 per 10,000 WY.

Several epidemiology studies indicate that third generation oral contraceptives, including those containing desogestrel (etonogestrel, the progestin in NuvaRing, is the biologically active metabolite of desogestrel), may be associated with a higher risk of VTE than oral contraceptives containing other progestins. Some of these studies indicate an approximate two-fold increased risk. However, data from other studies have not shown this two-fold increase in risk.

Use of CHCs also increases the risk of arterial thromboses such as strokes and myocardial infarctions, especially in women with other risk factors for these events. CHCs have been shown to increase both the relative and attributable risks of cerebrovascular events (thrombotic and hemorrhagic strokes). In general, the risk is greatest among older (>35 years of age), hypertensive women who also smoke.

Use NuvaRing with caution in women with cardiovascular disease risk factors.

5.2 Toxic Shock Syndrome (TSS)

Cases of TSS have been reported by NuvaRing users. TSS has been associated with tampons and certain barrier contraceptives, and, in some cases the NuvaRing users were also using tampons. A causal relationship between the use of NuvaRing and TSS has not been established. If a patient exhibits signs or symptoms of TSS, consider the possibility of this diagnosis and initiate appropriate medical evaluation and treatment.

5.3 Liver Disease

Impaired Liver Function

Do not use NuvaRing in women with liver disease such as acute viral hepatitis or severe (decompensated) cirrhosis of the liver [see Contraindications (4)]. Acute or chronic disturbances of liver function may necessitate the discontinuation of CHC use until markers of liver function return to normal and CHC causation has been excluded [see Use in Specific Populations (8.6)]. Discontinue NuvaRing use if jaundice develops.

Liver Tumors

NuvaRing is contraindicated in women with benign and malignant liver tumors [see Contraindications (4)]. Hepatic adenomas are associated with CHC use. An estimate of the attributable risk is 3.3 cases per 100,000 CHC users. Rupture of hepatic adenomas may cause death through intra-abdominal hemorrhage.

Studies have shown an increased risk of developing hepatocellular carcinoma in long term (>8 years) CHC users. However, the attributable risk of liver cancers in CHC users is less than one case per million users.

5.4 Risk of Liver Enzyme Elevations with Concomitant Hepatitis C Treatment

CHCs, such as NuvaRing, are contraindicated for use with Hepatitis C drug combinations containing ombitasvir/paritaprevir/ritonavir (with or without dasabuvir) [see Contraindications (4)]. Discontinue NuvaRing prior to starting therapy with the combination drug regimen ombitasvir/paritaprevir/ritonavir (with or without dasabuvir). NuvaRing can be restarted approximately 2 weeks following completion of treatment with this hepatitis C combination drug regimen.

During clinical trials with some HCV combination drug regimens, ALT elevations were observed in women using ethinyl estradiol containing medications [see Drug Interactions (7)]. For example, the Hepatitis C combination drug regimen that contains ombitasvir/paritaprevir/ritonavir, with and without dasabuvir, ALT elevations greater than 5 times the upper limit of normal (ULN), including some cases greater than 20 times the ULN, were significantly more frequent in women using ethinyl estradiol-containing medications, such as CHCs.

5.5 High Blood Pressure

NuvaRing is contraindicated in women with uncontrolled hypertension or hypertension with vascular disease [see Contraindications (4)]. For women with well-controlled hypertension, monitor blood pressure and stop NuvaRing use if blood pressure rises significantly.

An increase in blood pressure has been reported in women using CHCs and this increase is more likely in older women and with extended duration of use. The incidence of hypertension increases with increasing concentrations of progestin.

5.6 Hypersensitivity Reactions

Hypersensitivity reactions of anaphylaxis and angioedema have been reported during use of NuvaRing. If anaphylaxis and/or angioedema is suspected, NuvaRing should be discontinued and appropriate treatment administered. [See Contraindications (4).]

5.7 Vaginal Use

NuvaRing may not be suitable for women with conditions that make the vagina more susceptible to vaginal irritation or ulceration. Vaginal/cervical erosion or ulceration in women using NuvaRing has been reported. In some cases, the ring adhered to vaginal tissue, necessitating removal by a healthcare provider and in some instances (i.e., when the tissue had grown over the ring), removal was achieved by cutting the ring without incising the overlying vaginal tissue.

Some women are aware of the ring on occasion during the 21 days of use or during intercourse, and sexual partners may feel NuvaRing in the vagina.

5.8 Gallbladder Disease

Studies suggest a small increased relative risk of developing gallbladder disease among CHC users. Use of CHCs may also worsen existing gallbladder disease.

A past history of CHC-related cholestasis predicts an increased risk with subsequent CHC use. Women with a history of pregnancy-related cholestasis may be at an increased risk for CHC-related cholestasis.

5.9 Carbohydrate and Lipid Metabolic Effects

Carefully monitor prediabetic and diabetic women who are using NuvaRing. CHCs may decrease glucose tolerance.

Consider alternative contraception for women with uncontrolled dyslipidemia. Some women will have adverse lipid changes while on CHCs.

Women with hypertriglyceridemia, or a family history thereof, may be at an increased risk of pancreatitis when using CHCs.

5.10 Headache

If a woman using NuvaRing develops new headaches that are recurrent, persistent, or severe, evaluate the cause and discontinue NuvaRing if indicated.

Consider discontinuation of NuvaRing in the case of an increased frequency or severity of migraine during CHC use (which may be prodromal of a cerebrovascular event) [see Contraindications (4)].

5.11 Bleeding Irregularities and Amenorrhea

Unscheduled Bleeding and Spotting

Unscheduled bleeding (breakthrough or intracyclic) bleeding and spotting sometimes occur in women using CHCs, especially during the first three months of use. If bleeding persists or occurs after previously regular cycles, check for causes such as pregnancy or malignancy. If pathology and pregnancy are excluded, bleeding irregularities may resolve over time or with a change to a different CHC.

Bleeding patterns were evaluated in three large clinical studies. In the North American study (US and Canada, N=1,177), the percentages of subjects with breakthrough bleeding/spotting ranged from 7.2% to 11.7% during cycles 1-13. In the two non-US studies, the percentages of subjects with breakthrough bleeding/spotting ranged from 2.6% to 6.4% (Europe, N=1,145) and from 2.0% to 8.7% (Europe, Brazil, Chile, N=512).

Amenorrhea and Oligomenorrhea

If scheduled (withdrawal) bleeding does not occur, consider the possibility of pregnancy. If the patient has not adhered to the prescribed dosing schedule, consider the possibility of pregnancy at the time of the first missed period and take appropriate diagnostic measures.

Occasional missed periods may occur with the appropriate use of NuvaRing. In the clinical studies, the percent of women who did not have withdrawal bleeding in a given cycle ranged from 0.3% to 3.8%.

If the patient has adhered to the prescribed regimen and misses two consecutive periods, rule out pregnancy.

Some women may experience amenorrhea or oligomenorrhea after discontinuing CHC use, especially when such a condition was pre-existent.

5.12 Inadvertent Urinary Bladder Insertion

There have been reports of inadvertent insertions of NuvaRing into the urinary bladder, which required cystoscopic removal. Assess for ring insertion into the urinary bladder in NuvaRing users who present with persistent urinary symptoms and are unable to locate the ring.

5.13 Depression

Carefully observe women with a history of depression and discontinue NuvaRing use if depression recurs to a serious degree.

5.14 Malignant Neoplasms

Breast Cancer

NuvaRing is contraindicated in females who currently have or have had breast cancer because breast cancer may be hormonally sensitive [see Contraindications (4)].

Epidemiology studies have not found a consistent association between use of combined oral contraceptives (COCs) and breast cancer risk. Studies do not show an association between ever (current or past) use of COCs and risk of breast cancer. However, some studies report a small increase in the risk of breast cancer among current or recent users (<6 months since last use) and current users with longer duration of COC use [see Postmarketing Experience (6.2)].

Cervical Cancer

Some studies suggest that CHCs are associated with an increase in the risk of cervical cancer or intraepithelial neoplasia. However, there is controversy about the extent to which these findings may be due to differences in sexual behavior and other factors.

5.15 Effect on Binding Globulins

The estrogen component of CHCs may raise the serum concentrations of thyroxine-binding globulin, sex hormone-binding globulin, and cortisol-binding globulin. The dose of replacement thyroid hormones or cortisol therapy may need to be increased.

5.16 Monitoring

A woman who is using NuvaRing should have a yearly visit with her healthcare provider for a blood pressure check and for other indicated healthcare.

5.17 Hereditary Angioedema

In women with hereditary angioedema, exogenous estrogens may induce or exacerbate symptoms of angioedema.

5.18 Chloasma

Chloasma may occasionally occur, especially in women with a history of chloasma gravidarum. Women with a tendency to chloasma should avoid exposure to the sun or ultraviolet radiation while using NuvaRing.

6 ADVERSE REACTIONS

The following serious adverse reactions with the use of CHCs are discussed elsewhere in the labeling.

- Serious cardiovascular events and stroke [see Boxed Warning and Warnings and Precautions (5.1)]
- Vascular events [see Warnings and Precautions (5.1)]
- Liver disease [see Warnings and Precautions (5.3)]

Adverse reactions commonly reported by CHC users are:

- Irregular uterine bleeding
- Nausea
- Breast tenderness
- Headache

6.1 Clinical Trials Experience

Because clinical trials are conducted under widely varying conditions, adverse reaction rates observed in the clinical trials of a drug cannot be directly compared to rates in the clinical trials of another drug and may not reflect the rates observed in practice.

Trials with a duration of 6 to 13 28-day cycles provided safety data. In total, 2,501 women, aged 18 to 41 contributed 24,520 cycles of exposure.

Common Adverse Reactions (≥ 2%): vaginitis (13.8%), headache (including migraine) (11.2%), mood changes (e.g., depression, mood swings, mood altered, depressed mood, affect lability) (6.4%), device-related events (e.g., expulsion/discomfort/foreign body sensation) (6.3%), nausea/vomiting (5.9%), vaginal discharge (5.7%), increased weight (4.9%), vaginal discomfort (4.0%), breast pain/discomfort/tenderness (3.8%), dysmenorrhea (3.5%), abdominal pain (3.2%), acne (2.4%), and decreased libido (2.0%).

Adverse Reactions (≥ 1%) Leading to Study Discontinuation: 13.0% of the women discontinued from the clinical trials due to an adverse reaction; the most common adverse reactions leading to discontinuation were device-related events (2.7%), mood changes (1.7%), headache (including migraine) (1.5%) and vaginal symptoms (1.2%).

Serious Adverse Reactions: deep vein thrombosis [see Warnings and Precautions (5.1)], anxiety, cholelithiasis, and vomiting.

6.2 Postmarketing Experience

Five studies that compared breast cancer risk between ever-users (current or past use) of COCs and never-users of COCs reported no association between ever use of COCs and breast cancer risk, with effect estimates ranging from 0.90 - 1.12 (Figure 2).

Three studies compared breast cancer risk between current or recent COC users (<6 months since last use) and never users of COCs (Figure 2). One of these studies reported no association between breast cancer risk and COC use. The other two studies found an increased relative risk of 1.19 - 1.33 with current or recent use. Both of these studies found an increased risk of breast cancer with current use of longer duration, with relative risks ranging from 1.03 with less than one year of COC use to approximately 1.4 with more than 8-10 years of COC use.

Figure 2: Relevant Studies of Risk of Breast Cancer with Combined Oral Contraceptives

RR = relative risk; OR = odds ratio; HR = hazard ratio. “ever COC” are females with current or past COC use; “never COC use” are females that never used COCs.

The following adverse reactions have been identified during post-approval use of NuvaRing. Because these reactions are reported voluntarily from a population of uncertain size, it is not always possible to reliably estimate their frequency or establish a causal relationship to drug exposure.

Immune system disorders: hypersensitivity reactions, including anaphylaxis and angioedema

Nervous system disorders: stroke/cerebrovascular accident

Vascular disorders: arterial events (including arterial thromboembolism and myocardial infarction), aggravation of varicose veins

Skin and subcutaneous tissue disorders: exacerbations of hereditary and acquired angioedema, urticaria, chloasma

Reproductive system and breast disorders: penile disorders, including local reactions on penis (in male partners of women using NuvaRing), galactorrhea

General disorders and administration site conditions: device breakage (including with concomitant use of intravaginal antimycotic, antibiotic, and lubricant products)

Injury, poisoning and procedural complications: vaginal injury (including associated pain, discomfort, and bleeding) associated with ring breakage

7 DRUG INTERACTIONS

Consult the labeling of all concurrently-used drugs to obtain further information about interactions with hormonal contraceptives or the potential for enzyme alterations.

7.1 Effects of Other Drugs on CHCs

Substances decreasing the plasma concentrations of CHCs and potentially diminishing the effectiveness of CHCs

Drugs or herbal products that induce certain enzymes, including cytochrome P450 3A4 (CYP3A4), may decrease the plasma concentrations of CHCs and potentially diminish the effectiveness of CHCs or increase breakthrough bleeding. Some drugs or herbal products that may decrease the effectiveness of hormonal contraceptives include: phenytoin, barbiturates, carbamazepine, bosentan, felbamate, griseofulvin, oxcarbazepine, rifampicin, topiramate, rifabutin, rufinamide, aprepitant, and products containing St. John's wort. Interactions between CHCs and other drugs may lead to breakthrough bleeding and/or contraceptive failure.

Counsel women to use an alternative non-hormonal method of contraception or a back-up method when enzyme inducers are used with NuvaRing, and to continue back-up non-hormonal contraception for 28 days after discontinuing the enzyme inducer to ensure contraceptive reliability.

Note: NuvaRing may interfere with the correct placement and position of certain female barrier methods such as a diaphragm or female condom. These methods are not recommended as back-up methods with NuvaRing use [see Dosage and Administration (2.5)].

The serum concentrations of etonogestrel and ethinyl estradiol were not affected by concomitant administration of oral amoxicillin or doxycycline in standard dosages during 10 days of antibiotic treatment. The effects of other antibiotics on etonogestrel or ethinyl estradiol concentrations have not been evaluated.

Substances increasing the plasma concentrations of CHCs

Co-administration of atorvastatin and certain CHCs containing ethinyl estradiol increase AUC values for ethinyl estradiol by approximately 20-25%. Ascorbic acid and acetaminophen may increase plasma ethinyl estradiol concentrations, possibly by inhibition of conjugation. Concomitant administration of strong or moderate CYP3A4 inhibitors such as itraconazole, voriconazole, fluconazole, grapefruit juice, or ketoconazole may increase plasma estrogen and/or progestin concentrations. Co-administration of vaginal miconazole nitrate and NuvaRing increases the serum concentrations of etonogestrel and ethinyl estradiol by up to 40% [see Clinical Pharmacology (12.3)].

Human immunodeficiency virus (HIV) / Hepatitis C Virus (HCV) protease inhibitors and non-nucleoside reverse transcriptase inhibitors

Significant changes in the plasma concentrations of the estrogen and /or progestin have been noted in some cases of co-administration with HIV protease inhibitors (decrease [e.g., nelfinavir, ritonavir, darunavir/ritonavir, (fos)amprenavir/ritonavir, lopinavir/ritonavir, and tipranavir/ritonavir] or increase [e.g., indinavir and atazanavir/ritonavir]) /HCV protease inhibitors (decrease [e.g., boceprevir and telaprevir]) or with non-nucleoside reverse transcriptase inhibitors (decrease [e.g., efavirenz, nevirapine] or increase [e.g., etravirine]). These changes may be clinically relevant in some cases.

7.2 Effects of CHCs on Other Drugs

CHCs containing ethinyl estradiol may inhibit the metabolism of other compounds (e.g., cyclosporine, prednisolone, theophylline, tizanidine, and voriconazole) and increase their plasma concentrations. CHCs have been shown to decrease plasma concentrations of acetaminophen, clofibric acid, morphine, salicylic acid and temazepam. A significant decrease in the plasma concentrations of lamotrigine has been shown, likely due to induction of lamotrigine glucuronidation. This may reduce seizure control; therefore, dosage adjustments of lamotrigine may be necessary.

Women on thyroid hormone replacement therapy may need increased doses of thyroid hormone because serum concentrations of thyroid-binding globulin increase with use of CHCs.

7.3 Concomitant Use with HCV Combination Therapy – Liver Enzyme Elevation

Do not co-administer NuvaRing with HCV drug combinations containing ombitasvir/paritaprevir/ritonavir, with or without dasabuvir, due to potential for ALT elevations. Concomitant use with some other HCV antiviral medicinal products, such as those containing glecaprevir/pibrentasvir, may increase the risk of ALT elevations [see Warnings and Precautions (5.4)].

7.4 Interference with Laboratory Tests

The use of contraceptive steroids may influence the results of certain laboratory tests, such as coagulation factors, lipids, glucose tolerance, and binding proteins.

8 USE IN SPECIFIC POPULATIONS

8.1 Pregnancy

Risk Summary

NuvaRing is contraindicated during pregnancy because there is no need for pregnancy prevention in a woman who is already pregnant. Epidemiologic studies and meta-analyses have not shown an increased risk of genital or non-genital birth defects (including cardiac anomalies and limb-reduction defects) following maternal exposure to low dose CHCs prior to conception or during early pregnancy. No adverse developmental outcomes were observed in pregnant rats and rabbits with the administration of etonogestrel during organogenesis at doses approximately 300 times the anticipated daily vaginal human dose (~0.002 mg/kg/day).

No adverse developmental outcomes were observed in pregnant rats and rabbits with the co-administration of the combination desogestrel/ethinyl estradiol during organogenesis at desogestrel/ethinyl estradiol doses at least 2/5 times, respectively, the anticipated daily vaginal human dose (~0.002 desogestrel/0.00025 ethinyl estradiol mg/kg/day).

Discontinue NuvaRing use if pregnancy is confirmed.

Data

Animal Data

In rats and rabbits at dosages up to 300 times the anticipated dose, etonogestrel is neither embryotoxic nor teratogenic. Co-administration of a maternally toxic dose of desogestrel/ethinyl estradiol to pregnant rats was associated with embryolethality and wavy ribs at a desogestrel/ethinyl estradiol dose that was 40/130 times, respectively, the anticipated vaginal human dose (0.002 desogestrel/0.00025 ethinyl estradiol mg/kg/day). No adverse embryofetal effects were observed when the combination was administered to pregnant rats at a desogestrel/ethinyl estradiol dose that was 4/13 times, respectively, the anticipated vaginal human dose. When desogestrel/ethinyl estradiol was given to pregnant rabbits, pre-implantation loss was observed at a desogestrel/ethinyl estradiol dose that was 3/10 times, respectively, the anticipated vaginal human dose. No adverse embryofetal effects were observed when the combination was administered to pregnant rabbits at a desogestrel/ethinyl estradiol dose that was 2/5 times the anticipated vaginal human dose.

8.2 Lactation

Risk Summary

Small amounts of contraceptive steroids and/or metabolites, including etonogestrel and ethinyl estradiol are transferred to human milk. Harmful effects have not been observed in breastfed infants exposed to CHCs through breast milk. CHCs can reduce milk production in breastfeeding mothers. This is less likely to occur once breastfeeding is well-established; however, it can occur at any time in some women.

When possible, advise the nursing mother to use non-estrogen-containing contraception until she has completely weaned her child. The developmental and health benefits of breastfeeding should be considered along with the mother's clinical need for NuvaRing and any potential adverse effects on the breastfed child from NuvaRing or from the underlying maternal condition.

8.4 Pediatric Use

Safety and efficacy of NuvaRing have been established in women of reproductive age. Efficacy is expected to be the same for postpubertal adolescents under the age of 18 and for users 18 years and older. Use of this product before menarche is not indicated.

8.5 Geriatric Use

NuvaRing has not been studied in postmenopausal women and is not indicated in this population.

8.6 Hepatic Impairment

The effect of hepatic impairment on the pharmacokinetics of NuvaRing has not been studied. Steroid hormones may be poorly metabolized in patients with impaired liver function. Acute or chronic disturbances of liver function may necessitate the discontinuation of CHC use until markers of liver function return to normal. [See Contraindications (4) and Warnings and Precautions (5.3).]

8.7 Renal Impairment

The effect of renal impairment on the pharmacokinetics of NuvaRing has not been studied.

10 OVERDOSAGE

There have been no reports of serious ill effects from overdose of CHCs. Overdosage may cause withdrawal bleeding in females and nausea. If the ring breaks, it does not release a higher dose of hormones. In case of suspected overdose, all NuvaRing rings should be removed and symptomatic treatment given.

11 DESCRIPTION

NuvaRing (etonogestrel/ethinyl estradiol vaginal ring) is a non-biodegradable, flexible, transparent, colorless to almost colorless, combination contraceptive vaginal ring containing two active components, a progestin, etonogestrel (13-ethyl-17-hydroxy-11-methylene-18,19-dinor-17α-pregn-4-en-20-yn-3-one) and an estrogen, ethinyl estradiol (19-nor-17α-pregna-1,3,5(10)-trien-20-yne-3,17-diol). When placed in the vagina, each ring releases on average 0.120 mg/day of etonogestrel and 0.015 mg/day of ethinyl estradiol over a three-week period of use. NuvaRing is made of ethylene vinylacetate copolymers (28% and 9% vinylacetate) and magnesium stearate and contains 11.7 mg etonogestrel and 2.7 mg ethinyl estradiol. NuvaRing is not made with natural rubber latex. NuvaRing has an outer diameter of 54 mm and a cross-sectional diameter of 4 mm. The molecular weights for etonogestrel and ethinyl estradiol are 324.46 and 296.40, respectively.

The structural formulas are as follows:

12 CLINICAL PHARMACOLOGY

12.1 Mechanism of Action

Combination hormonal contraceptives act by suppression of gonadotropins. Although the primary effect of this action is inhibition of ovulation, other alterations include changes in the cervical mucus (which increase the difficulty of sperm entry into the uterus) and the endometrium (which reduce the likelihood of implantation).

12.3 Pharmacokinetics

Absorption

Etonogestrel: Etonogestrel released by NuvaRing is rapidly absorbed. The bioavailability of etonogestrel after vaginal administration is approximately 100%. The serum etonogestrel and ethinyl estradiol concentrations observed during three weeks of NuvaRing use are summarized in Table 2.

Ethinyl estradiol: Ethinyl estradiol released by NuvaRing is rapidly absorbed. The bioavailability of ethinyl estradiol after vaginal administration is approximately 56%, which is comparable to that with oral administration of ethinyl estradiol. The serum ethinyl estradiol concentrations observed during three weeks of NuvaRing use are summarized in Table 2.

Table 2: Mean (SD) Serum Etonogestrel and Ethinyl Estradiol Concentrations (n=16)
 | 1 week | 2 weeks | 3 weeks
etonogestrel (pg/mL) | 1578 (408) | 1476 (362) | 1374 (328)
ethinyl estradiol (pg/mL) | 19.1 (4.5) | 18.3 (4.3) | 17.6 (4.3)

The pharmacokinetic profile of etonogestrel and ethinyl estradiol during use of NuvaRing is shown in Figure 3.

Figure 3: Mean Serum Concentration-Time Profile of Etonogestrel and Ethinyl Estradiol during Three Weeks of NuvaRing Use

The pharmacokinetic parameters of etonogestrel and ethinyl estradiol were determined during one cycle of NuvaRing use in 16 healthy female subjects and are summarized in Table 3.

Table 3: Mean (SD) Pharmacokinetic Parameters of NuvaRing (n=16)
Hormone | Cmax pg/mL | Tmax hr | t1/2 hr | CL L/hr
etonogestrel | 1716 (445) | 200.3 (69.6) | 29.3 (6.1) | 3.4 (0.8)
ethinyl estradiol | 34.7 (17.5) | 59.3 (67.5) | 44.7 (28.8) | 34.8 (11.6)
Cmax- maximum serum drug concentration
Tmax- time at which maximum serum drug concentration occurs
t1/2 - elimination half-life, calculated by 0.693/Kelim
CL - apparent clearance

Prolonged use of NuvaRing: The mean serum etonogestrel concentration at the end of the fourth week of continuous use of NuvaRing was 1272 ± 311 pg/mL compared to a mean concentration range of 1578 ± 408 to 1374 ± 328 pg/mL at the end of weeks one to three. The mean serum ethinyl estradiol concentration at the end of the fourth week of continuous use of NuvaRing was 16.8 ± 4.6 pg/mL compared to a mean concentration range of 19.1 ± 4.5 to 17.6 ± 4.3 pg/mL at the end of weeks one to three.

Distribution

Etonogestrel: Etonogestrel is approximately 32% bound to sex hormone-binding globulin (SHBG) and approximately 66% bound to albumin in blood.

Ethinyl estradiol: Ethinyl estradiol is highly but not specifically bound to serum albumin (98.5%) and induces an increase in the serum concentrations of SHBG.

Metabolism

In vitro data shows that both etonogestrel and ethinyl estradiol are metabolized in liver microsomes by the cytochrome P450 3A4 isoenzyme. Ethinyl estradiol is primarily metabolized by aromatic hydroxylation, but a wide variety of hydroxylated and methylated metabolites are formed. These are present as free metabolites and as sulfate and glucuronide conjugates. The hydroxylated ethinyl estradiol metabolites have weak estrogenic activity. The biological activity of etonogestrel metabolites is unknown.

Excretion

Etonogestrel and ethinyl estradiol are primarily eliminated in urine, bile and feces.

Drug Interactions

[See also Drug Interactions (7).]

The drug interactions of NuvaRing were evaluated in several studies.

A single-dose vaginal administration of an oil-based 1200-mg miconazole nitrate capsule increased the serum concentrations of etonogestrel and ethinyl estradiol by approximately 17% and 16%, respectively. Following multiple doses of 200 mg miconazole nitrate by vaginal suppository or vaginal cream, the mean serum concentrations of etonogestrel and ethinyl estradiol increased by up to 40%.

A single-dose vaginal administration of 100-mg water-based nonoxynol-9 spermicide gel did not affect the serum concentrations of etonogestrel or ethinyl estradiol.

The serum concentrations of etonogestrel and ethinyl estradiol were not affected by concomitant administration of oral amoxicillin or doxycycline in standard dosages during 10 days of antibiotic treatment.

Tampon Use

The use of tampons had no effect on serum concentrations of etonogestrel and ethinyl estradiol during use of NuvaRing [see Dosage and Administration (2.5)].

13 NONCLINICAL TOXICOLOGY

13.1 Carcinogenesis, Mutagenesis, Impairment of Fertility

Carcinogenesis

In a 24-month carcinogenicity study in rats with subdermal implants releasing 10 and 20 mcg etonogestrel per day, (approximately 0.3 and 0.6 times the systemic steady-state exposure of women using NuvaRing), no drug-related carcinogenic potential was observed.

Mutagenesis

Etonogestrel was not genotoxic in the in vitro Ames/Salmonella reverse mutation assay, the chromosomal aberration assay in Chinese hamster ovary cells or in the in vivo mouse micronucleus test.

Impairment of Fertility

A fertility study was conducted with etonogestrel in rats at approximately 600 times the anticipated daily vaginal human dose (~0.002 mg/kg/day). Treatment did not have any adverse effect on resulting litter parameters after cessation of treatment supporting the return to fertility after suppression with etonogestrel.

14 CLINICAL STUDIES

In three large one-year clinical trials enrolling 2,834 women aged 18-40 years, in North America, Europe, Brazil, and Chile, the racial distribution was 93% Caucasian, 5.0% Black, 0.8% Asian, and 1.2% Other. Women with BMI ≥ 30 kg/m^2 were excluded from these studies.

Based on pooled data from the three trials, 2,356 women aged < 35 years completed 23,515 evaluable cycles of NuvaRing use (cycles in which no back-up contraception was used). The pooled pregnancy rate (Pearl Index) was 1.28 (95% CI [0.8, 1.9]) per 100 women-years of NuvaRing use. In the US study, the Pearl Index was 2.02 (95% CI [1.1, 3.4]) per 100 women-years of NuvaRing use.

Study data indicate the return of ovulation and spontaneous menstrual cycles in most women within a month after discontinuation of NuvaRing use.

15 REFERENCES

1. Dinger, J et. al., Cardiovascular risk associated with the use of an etonogestrel-containing vaginal ring. Obstetrics & Gynecology 2013; 122(4): 800-808.
2. Sidney, S. et. al., Recent combined hormonal contraceptives (CHCs) and the risk of thromboembolism and other cardiovascular events in new users. Contraception 2013; 87: 93–100.
3. Combined hormonal contraceptives (CHCs) and the risk of cardiovascular endpoints. Sidney, S. (primary author) http://www.fda.gov/downloads/Drugs/DrugSafety/UCM277384.pdf, accessed 23-Aug-2013.

16 HOW SUPPLIED/STORAGE AND HANDLING

Each NuvaRing (etonogestrel/ethinyl estradiol vaginal ring) is individually packaged in a reclosable aluminum laminate sachet consisting of three layers, from outside to inside: polyester, aluminum foil, and low-density polyethylene. The ring should be replaced in this reclosable sachet after use and discarded in a waste receptacle out of the reach of children and pets. It should not be flushed down the toilet.

Box of 3 sachets | NDC 78206-146-03

16.1 Storage

Prior to dispensing to the user, store refrigerated 2°C to 8°C (36°F to 46°F). After dispensing to the user, NuvaRing can be stored for up to 4 months at 25°C (77°F); excursions permitted to 15°C to 30°C (59°F to 86°F) [see USP Controlled Room Temperature].

Avoid storing NuvaRing in direct sunlight or at temperatures above 30°C (86°F).

For the Dispenser: When NuvaRing is dispensed to the user, place an expiration date on the label. The date should not exceed either 4 months from the date of dispensing or the expiration date, whichever comes first.

17 PATIENT COUNSELING INFORMATION

Advise the patient to read the FDA-approved patient labeling (Patient Information and Instructions for Use).

Counsel patients regarding the following:

Increased risk of cardiovascular events

- Advise patients that cigarette smoking increases the risk of serious cardiovascular events from use of NuvaRing, and women who are over 35 years old and smoke should not use NuvaRing [see Boxed Warning].
- Inform patients that the increased risk of VTE compared to non-users of CHCs is greatest after initially starting a CHC or restarting (following a 4-week or greater CHC-free interval) the same or a different CHC [see Warnings and Precautions (5.1)].

Use and administration

- Inform patients that NuvaRing does not protect against HIV infection (AIDS) and other sexually transmitted infections.
- Advise patients on the proper usage of NuvaRing and what to do if she does not comply with the labeled timing of insertion and removal [see Dosage and Administration (2)].
- Advise patients to regularly check for the presence of NuvaRing in the vagina (for example, before and after intercourse) [see Dosage and Administration (2.3)].

Pregnancy

- Inform patients that NuvaRing is not to be used during pregnancy. If pregnancy is planned or occurs during treatment with NuvaRing, instruct the patient to discontinue NuvaRing use [see Use in Specific Populations (8.1)].

Use of additional contraception

- Inform patients that they need to use a barrier method of contraception when the ring is out for more than three continuous hours until NuvaRing has been used continuously for at least seven days [see Dosage and Administration (2.3)].
- Advise patients to use a back-up or alternative method of contraception when enzyme inducers are used with NuvaRing [see Drug Interactions (7.1)].
- Inform patients who start NuvaRing postpartum and have not yet had a normal period that they should use an additional non-hormonal method of contraception for the first seven days [see Dosage and Administration (2.2)].

Lactation

- Inform patients that CHCs may reduce breast milk production. This is less likely to occur if breastfeeding is well established [see Use in Specific Populations (8.2)].

Amenorrhea

- Inform patients that amenorrhea may occur. Rule out pregnancy in the event of amenorrhea if NuvaRing has been out of the vagina for more than three consecutive hours, if the ring-free interval was extended beyond one week, if the woman has missed a period for two or more consecutive cycles, and if the ring has been retained for longer than four weeks [see Warnings and Precautions (5.11)].

Disposal

- Advise patients on the proper disposal of a used NuvaRing [see How Supplied/Storage and Handling (16)].

Manufactured for: Organon USA LLC, a subsidiary of
ORGANON & Co.,
Jersey City, NJ 07302, USA

Manufactured by: N.V. Organon, Oss, The Netherlands, a subsidiary of Organon & Co., Jersey City, NJ 07302, USA

For patent information: www.organon.com/our-solutions/patent/

© 2024 Organon group of companies. All rights reserved.

uspi-og8342a-rng-2412r006

Patient Information

NuvaRing® (NEW-vah-ring)
(etonogestrel/ethinyl estradiol vaginal ring)

What is the most important information I should know about NuvaRing?

Do not use NuvaRing if you smoke cigarettes and are over 35 years old. Smoking increases your risk of serious cardiovascular side effects (heart and blood vessel problems) from combination hormonal contraceptives (CHCs), including death from heart attack, blood clots or stroke. This risk increases with age and the number of cigarettes you smoke.

Hormonal birth control methods help to lower the chances of becoming pregnant. They do not protect against HIV infection (AIDS) and other sexually transmitted infections.

What is NuvaRing?

NuvaRing (NEW-vah-ring) is a flexible birth control vaginal ring used to prevent pregnancy.

NuvaRing contains a combination of a progestin and estrogen, 2 kinds of female hormones. Birth control methods that contain both an estrogen and a progestin are called combination hormonal contraceptives (CHCs).

How well does NuvaRing work?

Your chance of getting pregnant depends on how well you follow the directions for using NuvaRing. The better you follow the directions, the less chance you have of getting pregnant.

Based on the results of a US clinical study, approximately 1 to 3 women out of 100 women may get pregnant during the first year they use NuvaRing.

The following chart shows the chance of getting pregnant for women who use different methods of birth control. Each box on the chart contains a list of birth control methods that are similar in effectiveness. The most effective methods are at the top of the chart. The box on the bottom of the chart shows the chance of getting pregnant for women who do not use birth control and are trying to get pregnant.

Who should not use NuvaRing?

Do not use NuvaRing if you:

- smoke and are over 35 years old
- have or have had blood clots in your arms, legs, eyes, or lungs
- have an inherited problem with your blood that makes it clot more than normal
- have had a stroke
- have had a heart attack
- have certain heart valve problems or heart rhythm problems that can cause blood clots to form in the heart
- have high blood pressure that medicine can't control
- have diabetes with kidney, eye, nerve, or blood vessel damage
- have certain kinds of severe migraine headaches with aura, numbness, weakness, or changes in vision, or have any migraine headaches if you are over age 35
- have liver disease, including liver tumors
- take any Hepatitis C drug combination containing ombitasvir/paritaprevir/ritonavir, with or without dasabuvir. This may increase levels of the liver enzyme "alanine aminotransferase" (ALT) in the blood
- have unexplained vaginal bleeding
- are pregnant or think you may be pregnant. NuvaRing is not for pregnant women.
- have or have had breast cancer or any cancer that is sensitive to female hormones
- are allergic to etonogestrel, ethinyl estradiol or any of the ingredients in NuvaRing. See the list of ingredients in NuvaRing at the end of this leaflet.

Hormonal birth control methods may not be a good choice for you if you have ever had jaundice (yellowing of the skin or eyes) caused by pregnancy or related to previous use of hormonal birth control.

Tell your healthcare provider if you have ever had any of the conditions listed above. Your healthcare provider can suggest another method of birth control.

What should I tell my healthcare provider before using NuvaRing?

Before you use NuvaRing tell your healthcare provider if you:

- have any medical conditions
- smoke
- are pregnant or think you are pregnant
- recently had a baby
- recently had a miscarriage or abortion
- have a family history of breast cancer
- have or have had breast nodules, fibrocystic disease, an abnormal breast X-ray, or abnormal mammogram
- use tampons and have a history of toxic shock syndrome
- have been diagnosed with depression
- have had liver problems including jaundice during pregnancy
- have or have had elevated cholesterol or triglycerides
- have or have had gallbladder, liver, heart, or kidney disease
- have diabetes
- have a history of jaundice (yellowing of the skin or eyes) caused by pregnancy (also called cholestasis of pregnancy)
- have a history of scanty or irregular menstrual periods
- have any condition that makes the vagina become irritated easily
- have or have had high blood pressure
- have or have had migraines or other headaches or seizures
- are scheduled for surgery. NuvaRing may increase your risk of blood clots after surgery. You should stop using NuvaRing at least 4 weeks before you have surgery and not restart it until at least 2 weeks after your surgery.
- are scheduled for any laboratory tests. Certain blood tests may be affected by hormonal birth control methods.
- are breastfeeding or plan to breastfeed. Hormonal birth control methods that contain estrogen, like NuvaRing, may decrease the amount of milk you make. A small amount of hormones from NuvaRing may pass into your breast milk. Consider another non-hormonal method of birth control until you are ready to stop breastfeeding.
- have (or have ever had) an allergic reaction while using NuvaRing, including hives, swelling of the face, lips, tongue, and/or throat causing difficulty in breathing or swallowing (anaphylaxis and/or angioedema).
- have a family history of angioedema. Products containing estrogens may cause or worsen these symptoms.

Tell your healthcare provider about all medicines and herbal products you take, including prescription and over-the-counter medicines, vitamins and herbal supplements.

Some medicines and herbal products may make hormonal birth control less effective, including, but not limited to:

- certain anti-seizure medicines (such as barbiturates, carbamazepine, felbamate, oxcarbazepine, phenytoin, rufinamide and topiramate)
- medicine to treat fungal infections (griseofulvin)
- certain combinations of HIV medicines, (such as nelfinavir, ritonavir, darunavir/ritonavir, (fos)amprenavir/ritonavir, lopinavir/ritonavir, and tipranavir/ritonavir)
- certain Hepatitis C (HCV) medicines (such as boceprevir and telaprevir)
- non-nucleoside reverse transcriptase inhibitors (such as efavirenz and nevirapine)
- medicine to treat tuberculosis (such as rifampicin and rifabutin)
- medicine to treat high blood pressure in the vessels of the lung (bosentan)
- medicine to treat chemotherapy-induced nausea and vomiting (aprepitant)
- St John's wort

Use an additional barrier contraceptive method (such as a male condom with spermicide) when you take medicines that may make NuvaRing less effective. Since the effect of another medicine on NuvaRing may last up to 28 days after stopping the medicine, it is necessary to use the additional barrier contraceptive method for that long to help prevent you from becoming pregnant. While using NuvaRing, you should not use certain female barrier contraceptive methods such as a vaginal diaphragm, cervical cap or female condom as your back-up method of birth control because NuvaRing may interfere with the correct placement and position of a diaphragm, cervical cap or female condom.

Some medicines and grapefruit juice may increase the level of ethinyl estradiol in your blood if used together, including:

- the pain reliever acetaminophen
- ascorbic acid (vitamin C)
- medicines that affect how your liver breaks down other medicines (such as itraconazole, ketoconazole, voriconazole, fluconazole, clarithromycin, erythromycin, and diltiazem)
- certain HIV medicines (atazanavir/ritonavir and indinavir)
- non-nucleoside reverse transcriptase inhibitors (such as etravirine)
- medicines to lower cholesterol such as atorvastatin and rosuvastatin

Hormonal birth control methods may interact with lamotrigine, a medicine used for seizures. This may increase the risk of seizures, so your healthcare provider may need to adjust your dose of lamotrigine.

Women on thyroid replacement therapy may need increased doses of thyroid hormone.

Some Hepatitis C drug combinations (such as glecaprevir/pibrentasvir) may increase levels of the liver enzyme “alanine aminotransferase” (ALT) in the blood.

Ask your healthcare provider if you are not sure if you take any of the medicines listed above. Know the medicines you take. Keep a list of them to show your doctor and pharmacist when you get a new medicine.

How should I use NuvaRing?

- Read the Instructions for Use at the end of this Patient Information that comes with your NuvaRing for information about the right way to use NuvaRing.
- Use NuvaRing exactly as your healthcare provider tells you to use it.
- NuvaRing is used in a 4-week cycle.
  - Insert 1 NuvaRing in the vagina and keep it in place for 3 weeks (21 days).
    Regularly check that NuvaRing is in your vagina (for example, before and after intercourse) to ensure that you are protected from pregnancy.
  - Remove the NuvaRing for a 1-week break (7 days). During the 1-week break (7 days), you will usually have your menstrual period.
    Note: Insert and remove NuvaRing on the same day of the week and at the same time:
    - For example, if you insert your NuvaRing on a Monday at 8:00 am, you should remove it on the Monday 3 weeks later at 8:00 am.
    - After your 1-week (7 days) break, you should insert a new NuvaRing on the next Monday at 8:00 am.
- While using NuvaRing, you should not use certain female barrier contraceptive methods such as a vaginal diaphragm, cervical cap or female condom as your back-up method of birth control because NuvaRing may interfere with the correct placement and position of a diaphragm, cervical cap or female condom.
- Ring breakage has occurred when also using a vaginal product such as a lubricant or treatment for infection (see "What should I do if my NuvaRing comes out of my vagina?"). Use of spermicides or vaginal yeast products will not make NuvaRing less effective at preventing pregnancy.
- Use of tampons will not make NuvaRing less effective or stop NuvaRing from working.
- If NuvaRing has been left inside your vagina for more than 4 weeks (28 days), you may not be protected from pregnancy and you should see your healthcare provider to be sure you are not pregnant. Until you know the results of your pregnancy test, you should use an extra method of birth control, such as male condoms with spermicide, until the new NuvaRing has been in place for 7 days in a row.
- Do not use more than 1 NuvaRing at a time. Too much hormonal birth control medicine in your body may cause nausea, vomiting, or vaginal bleeding.

Your healthcare provider should examine you at least 1 time a year to see if you have any signs of side effects from using NuvaRing.

What are the possible side effects of using NuvaRing?

See "What is the most important information I should know about NuvaRing?"

NuvaRing may cause serious side effects, including:

blood clots. Like pregnancy, combination hormonal birth control methods increase the risk of serious blood clots (see following graph), especially in women who have other risk factors, such as smoking, obesity, or age greater than 35. This increased risk is highest when you first start using a combination hormonal birth control method or when you restart the same or different combination hormonal birth control method after not using it for a month or more. Talk with your healthcare provider about your risk of getting a blood clot before using NuvaRing or before deciding which type of birth control is right for you.
In some studies of women who used NuvaRing, the risk of getting a blood clot was similar to the risk in women who used combination birth control pills.
Other studies have reported that the risk of blood clots was higher for women who use combination birth control pills containing desogestrel (a progestin similar to the progestin in NuvaRing) than for women who use combination birth control pills that do not contain desogestrel.
It is possible to die or be permanently disabled from a problem caused by a blood clot, such as heart attack or stroke. Some examples of serious blood clots are blood clots in the:
  - legs (deep vein thrombosis)
  - lungs (pulmonary embolus)
  - eyes (loss of eyesight)
  - heart (heart attack)
  - brain (stroke)
To put the risk of developing a blood clot into perspective: If 10,000 women who are not pregnant and do not use hormonal birth control are followed for one year, between 1 and 5 of these women will develop a blood clot. The figure below shows the likelihood of developing a serious blood clot for women who are not pregnant and do not use hormonal birth control, for women who use hormonal birth control, for pregnant women, and for women in the first 12 weeks after delivering a baby.
  Likelihood of Developing a Serious Blood Clot (Venous Thromboembolism [VTE])
  *CHC=combination hormonal contraception
  **Pregnancy data based on actual duration of pregnancy in the reference studies. Based on a model assumption that pregnancy duration is nine months, the rate is 7 to 27 per 10,000 WY.
Call your healthcare provider right away if you have:
  - leg pain that does not go away
  - sudden shortness of breath
  - sudden blindness, partial or complete
  - severe pain or pressure in your chest
  - sudden, severe headache unlike your usual headaches
  - weakness or numbness in an arm or leg, or trouble speaking
  - yellowing of the skin or eyeballs

Other serious risks include:

- Toxic Shock Syndrome (TSS). Some of the symptoms are much the same as the flu, but they can become serious very quickly. Call your healthcare provider or get emergency treatment right away if you have the following symptoms:
  - sudden high fever
  - vomiting
  - diarrhea
  - a sunburn-like rash
  - muscle aches
  - dizziness
  - fainting or feeling faint when standing up
- allergic reaction, including hives, swelling of the face, lips, tongue, and/or throat causing difficulty in breathing or swallowing (anaphylaxis and/or angioedema)
- liver problems, including liver tumors
- high blood pressure
- gallbladder problems
- accidental insertion into bladder
- symptoms of a problem called angioedema if you already have a (family) history of angioedema

The most common side effects of NuvaRing are:

- tissue irritation inside your vagina or on your cervix
- headache (including migraine)
- mood changes (including depression, especially if you had depression in the past). Call your healthcare provider immediately if you have any thoughts of harming yourself.
- NuvaRing problems, including the ring slipping out or causing discomfort
- nausea and vomiting
- vaginal discharge
- weight gain
- vaginal discomfort
- breast pain, discomfort, or tenderness
- painful menstrual periods
- abdominal pain
- acne
- less sexual desire

Some women have spotting or light bleeding during NuvaRing use. If these symptoms occur, do not stop using NuvaRing. The problem will usually go away. If it doesn't go away, check with your healthcare provider.

Other side effects seen with NuvaRing include breast discharge; vaginal injury (including pain, discomfort, and bleeding) associated with broken rings; and penis discomfort of the partner (such as irritation, rash, itching).

Less common side effects seen with combination hormonal birth control include:

- Blotchy darkening of your skin, especially on your face
- High blood sugar, especially in women who already have diabetes
- High fat (cholesterol, triglycerides) levels in the blood

There have been reports of the ring becoming stuck to the vaginal tissue and having to be removed by a healthcare provider. Call your healthcare provider if you are unable to remove your NuvaRing.

Tell your healthcare provider about any side effect that bothers you or that does not go away. These are not all the possible side effects of NuvaRing. For more information, ask your healthcare provider or pharmacist. Call your healthcare provider for medical advice about side effects. You may report side effects to FDA at 1-800-FDA-1088.

How should I store NuvaRing and throw away used NuvaRings?

- Store NuvaRing at room temperature between 68°F to 77°F (20°C to 25°C).
- Store NuvaRing at room temperature for up to 4 months after you receive it. Throw NuvaRing away if the expiration date on the label has passed.
- Do not store NuvaRing above 86°F (30°C).
- Avoid direct sunlight.
- Place the used NuvaRing in the re-closable foil pouch and properly throw it away in your household trash out of the reach of children and pets. Do not flush your used NuvaRing down the toilet.

Keep NuvaRing and all medicines out of the reach of children.

General information about the safe and effective use of NuvaRing

Medicines are sometimes prescribed for purposes other than those listed in the Patient Information. Do not use NuvaRing for a condition for which it was not prescribed. Do not give NuvaRing to other people. It may harm them.

This leaflet summarizes the most important information about NuvaRing. If you would like more information, talk with your healthcare provider. You can ask your pharmacist or healthcare provider for information about NuvaRing that is written for health professionals.

For more information on NuvaRing, go to www.nuvaring.com or call 1-844-674-3200.

What are the ingredients in NuvaRing?

Active ingredients: etonogestrel and ethinyl estradiol

Inactive ingredients: ethylene vinylacetate copolymers (28% and 9% vinylacetate) and magnesium stearate.

NuvaRing is not made with natural rubber latex.

Does hormonal birth control cause cancer?

It is not known if hormonal birth control causes breast cancer. Some studies, but not all, suggest that there could be a slight increase in the risk of breast cancer among current users with longer duration of use.

If you have breast cancer now, or have had it in the past, do not use hormonal birth control because some breast cancers are sensitive to hormones.

Women who use hormonal birth control methods may have a slightly higher chance of getting cervical cancer. However, this may be due to other reasons such as having more sexual partners.

What should I know about my period when using NuvaRing?

When you use NuvaRing you may have bleeding and spotting between periods, called unplanned bleeding. Unplanned bleeding may vary from slight staining between menstrual periods to breakthrough bleeding, which is a flow much like a regular period. Unplanned bleeding occurs most often during the first few months of NuvaRing use, but may also occur after you have been using NuvaRing for some time. Such bleeding may be temporary and usually does not indicate any serious problems. It is important to continue using the ring on schedule. If the unplanned bleeding or spotting is heavy or lasts for more than a few days, you should discuss this with your healthcare provider.

What if I miss my regular scheduled period when using NuvaRing?

Some women miss periods on hormonal birth control, even when they are not pregnant. Consider the possibility that you may be pregnant if:

1. you miss a period and NuvaRing was out of the vagina for more than 3 hours during the 3 weeks (21 days) of ring use
2. you miss a period and waited longer than 1 week to insert a new ring
3. you have followed the instructions and you miss 2 periods in a row
4. you have left NuvaRing in place for longer than 4 weeks (28 days)

What if I want to become pregnant?

You may stop using NuvaRing whenever you wish. Consider a visit with your healthcare provider for a pre-pregnancy checkup before you stop using NuvaRing.

Instructions for Use

NuvaRing (NEW-vah-ring)
(etonogestrel/ethinyl estradiol vaginal ring)

Read these Instructions for Use before you start using NuvaRing and each time you get a refill. There may be new information. This information does not take the place of talking to your healthcare provider about your treatment.

How should I start using NuvaRing?

If you are not currently using hormonal birth control, you have 2 ways to start using NuvaRing. Choose the best way for you:

- First Day Start: Insert NuvaRing on the first day of your menstrual period. You will not need to use another birth control method since you are using NuvaRing on the first day of your menstrual period.
- Day 2 to Day 5 Cycle Start: You may choose to start NuvaRing on days 2 to 5 of your menstrual period. Make sure you also use an extra method of birth control (barrier method), such as male condoms with spermicide for the first 7 days of NuvaRing use in the first cycle.

If you are changing from a birth control pill or patch to NuvaRing:

If you have been using your birth control method correctly and are certain that you are not pregnant, you can change to NuvaRing any day. Do not start NuvaRing any later than the day you would start your next birth control pill or apply your patch.

If you are changing from a progestin-only birth control method, such as a minipill, implant or injection or from an intrauterine system (IUS):

- You may switch from a minipill on any day. Start using NuvaRing on the day that you would have taken your next minipill.
- You should switch from an implant or the IUS and start using NuvaRing on the day that you remove the implant or IUS.
- You should switch from an injectable and start using NuvaRing on the day when your next injection would be due.

If you are changing from a minipill, implant or injection or from an intrauterine system (IUS), you should use an extra method of birth control, such as a male condom with spermicide during the first 7 days of using NuvaRing.

If you start using NuvaRing after an abortion or miscarriage:

- Following a first trimester abortion or miscarriage: You may start NuvaRing within 5 days following a first trimester abortion or miscarriage (the first 12 weeks of pregnancy). You do not need to use an additional birth control method.
- If you do not start NuvaRing within 5 days after a first trimester abortion or miscarriage, use a non-hormonal birth control method, such as male condoms and spermicide, while you wait for your period to start. Begin NuvaRing at the time of your next menstrual period. Count the first day of your menstrual period as "Day 1" and start NuvaRing one of the following 2 ways below.
  - First Day Start: Insert NuvaRing on the first day of your menstrual period. You will not need to use another birth control method since you are using NuvaRing on the first day of your menstrual period.
  - Day 2 to Day 5 Cycle Start: You may choose to start NuvaRing on Days 2 to 5 of your menstrual period. Make sure you also use an extra method of birth control (barrier method), such as male condoms with spermicide for the first 7 days of NuvaRing use in the first cycle.
- Following a second trimester abortion or miscarriage: You may start using NuvaRing no sooner than 4 weeks (28 days) after a second trimester abortion (after the first 12 weeks of pregnancy).

If you are starting NuvaRing after childbirth:

- You may start using NuvaRing no sooner than 4 weeks (28 days) after having a baby if you are not breastfeeding.
- If you have not gotten your menstrual period after childbirth, you should talk to your healthcare provider. You may need a pregnancy test to make sure you are not pregnant before you start using NuvaRing.
- Use another birth control method such as male condoms with spermicide for the first 7 days in addition to NuvaRing.

If you are breastfeeding you should not use NuvaRing. Use other birth control methods until you are no longer breastfeeding.

Step 1. Choose a position for insertion of NuvaRing.

- Choose the position that is comfortable for you. For example, lying down, squatting, or standing with 1 leg up (See Figures A, B, and C).

Positions for NuvaRing insertion

Step 2. Open the pouch to remove your NuvaRing.

- Each NuvaRing comes in a re-sealable foil pouch.
- Wash and dry your hands before removing NuvaRing from the foil pouch.
- Open the foil pouch at either notch near the top.
- Keep the foil pouch so you can place your used NuvaRing in it before you throw it away in your household trash.

Step 3. Prepare NuvaRing for insertion.

- Hold NuvaRing between your thumb and index finger and press the sides of the ring together (See Figures D and E).

Step 4. Insert NuvaRing into your vagina.

- Insert the folded NuvaRing into your vagina and gently push it further up into your vagina using your index finger (See Figures F and G).
- When you insert NuvaRing it may be in different positions in your vagina, but NuvaRing does not have to be in an exact position for it to work (See Figures H and I).
- NuvaRing may move around slightly within your vagina. This is normal. Although some women may be aware of NuvaRing in the vagina, most women do not feel it when it is in place.

Figure F

Figure G

Figure H

Figure I

Inserting NuvaRing (Figure F, Figure G) and positioning NuvaRing (Figure H, Figure I)

Note:

- If the NuvaRing feels uncomfortable, you may not have pushed the ring into your vagina far enough. Use your finger to gently push the NuvaRing as far as you can into your vagina. There is no danger of NuvaRing being pushed too far up in the vagina or getting lost (See Figure G).
- Some women have accidentally inserted NuvaRing into their bladder. If you have pain during or after insertion and you cannot find NuvaRing in your vagina, call your healthcare provider right away.
- Regularly check that NuvaRing is in your vagina (for example, before and after intercourse) to ensure you are protected from pregnancy.

Step 5. How do I remove NuvaRing?

- Wash and dry your hands.
- Choose the position that is most comfortable for you (See Figures A, B, and C).
- Put your index finger into your vagina and hook it through the NuvaRing. Gently pull downward and forward to remove the NuvaRing and pull it out (See Figure J).

Step 6. Throw away the used NuvaRing.

- Place the used NuvaRing in the re-sealable foil pouch and put it in a trash can out of the reach of children and pets.
- Do not throw NuvaRing in the toilet.

What else should I know about using NuvaRing?

What if I leave NuvaRing in too long?

- If you leave NuvaRing in your vagina for up to 4 weeks (28 days) you will still be getting pregnancy protection. Remove your old NuvaRing for 1 week (7 days) and insert a new NuvaRing 1 week (7 days) later (See Steps 1 through 4).
- If you leave NuvaRing in your vagina longer than 4 weeks (28 days), remove the ring and check to make sure you are not pregnant.
  If you are not pregnant, insert a new NuvaRing (See Steps 1 through 4). You must use another birth control method, such as male condoms with spermicide, until the new NuvaRing has been used for 7 days in a row.

What should I do if my NuvaRing comes out of my vagina?

NuvaRing can slip or accidentally come out (expelled) of your vagina, for example, during sexual intercourse, bowel movements, use of tampons, or if it breaks.

- NuvaRing may break causing the ring to lose its shape. If the ring stays in your vagina this should not lower NuvaRing's effectiveness at preventing pregnancy.
  - If NuvaRing breaks and slips out of your vagina, throw the broken ring in your household trash out of the reach of children and pets.
  - Insert a new NuvaRing (See Steps 1 through 4).
- You should pay attention when removing a tampon to be sure that your NuvaRing is not accidentally pulled out.
  - Be sure to insert NuvaRing before inserting a tampon.
  - If you accidentally pull out your NuvaRing while using tampons, rinse your NuvaRing in cool to lukewarm (not hot) water and insert it again right away.
- NuvaRing can be pushed out of (expelled from) your vagina, for example, during sexual intercourse or during a bowel movement.
  - If the expelled ring has been out of your vagina for less than 3 hours, rinse the expelled NuvaRing in cool to lukewarm (not hot) water and insert it again right away.
  - If the expelled NuvaRing has been out of your vagina for more than 3 continuous hours:
    - During Weeks 1 and 2, you may not be protected from pregnancy. Reinsert the ring as soon as you remember (See Steps 1 through 4). Use another birth control method, such as male condoms with spermicide, until the ring has been in place for 7 days in a row.
    - During Week 3, do not reinsert the NuvaRing that has been out of your vagina; but throw it away in your household trash away from children and pets. Use another birth control method, such as male condoms with spermicide, until the new NuvaRing has been used for 7 days in a row, following one of the two options below:
      - Option 1. Insert a new ring right away to start your next 21 Day NuvaRing use cycle. You may not have your regular period, but you may have spotting or vaginal bleeding.
      - Option 2. Insert a new ring no later than 7 days from the time the previous ring was removed or expelled. During this time, you may have your period.
    Note: You should only choose to do option 2 if you used NuvaRing for 7 days in a row, prior to the day that your previous NuvaRing was accidentally removed or expelled.
- If NuvaRing was out of the vagina for an unknown amount of time, you may not be protected from pregnancy. Perform a pregnancy test prior to inserting a new ring and consult your healthcare provider.

This Patient Information and Instructions for Use have been approved by the U.S. Food and Drug Administration.

Manufactured for: Organon USA LLC, a subsidiary of
ORGANON & Co.,
Jersey City, NJ 07302, USA

Manufactured by: N.V. Organon, Oss, The Netherlands, a subsidiary of
Organon & Co., Jersey City, NJ 07302, USA

For patent information: www.organon.com/our-solutions/patent/

© 2024 Organon group of companies. All rights reserved.

Revised: 12/2024

usppi-og8342a-rng-2412r005

PRINCIPAL DISPLAY PANEL - 3 Ring Pouch Carton

For the Dispenser: Store refrigerated 2°C to 8°C (36°F to 46°F).

NDC 78206-146-03

NUVARING®
(etonogestrel/ethinyl estradiol vaginal ring)
delivers 0.120 mg/0.015 mg per day

For Vaginal Use

Keep out of the reach of children.

This product is intended to prevent
pregnancy. It does not protect against
HIV infection (AIDS) and other sexually
transmitted diseases.

Rx only

Contains 3 Rings